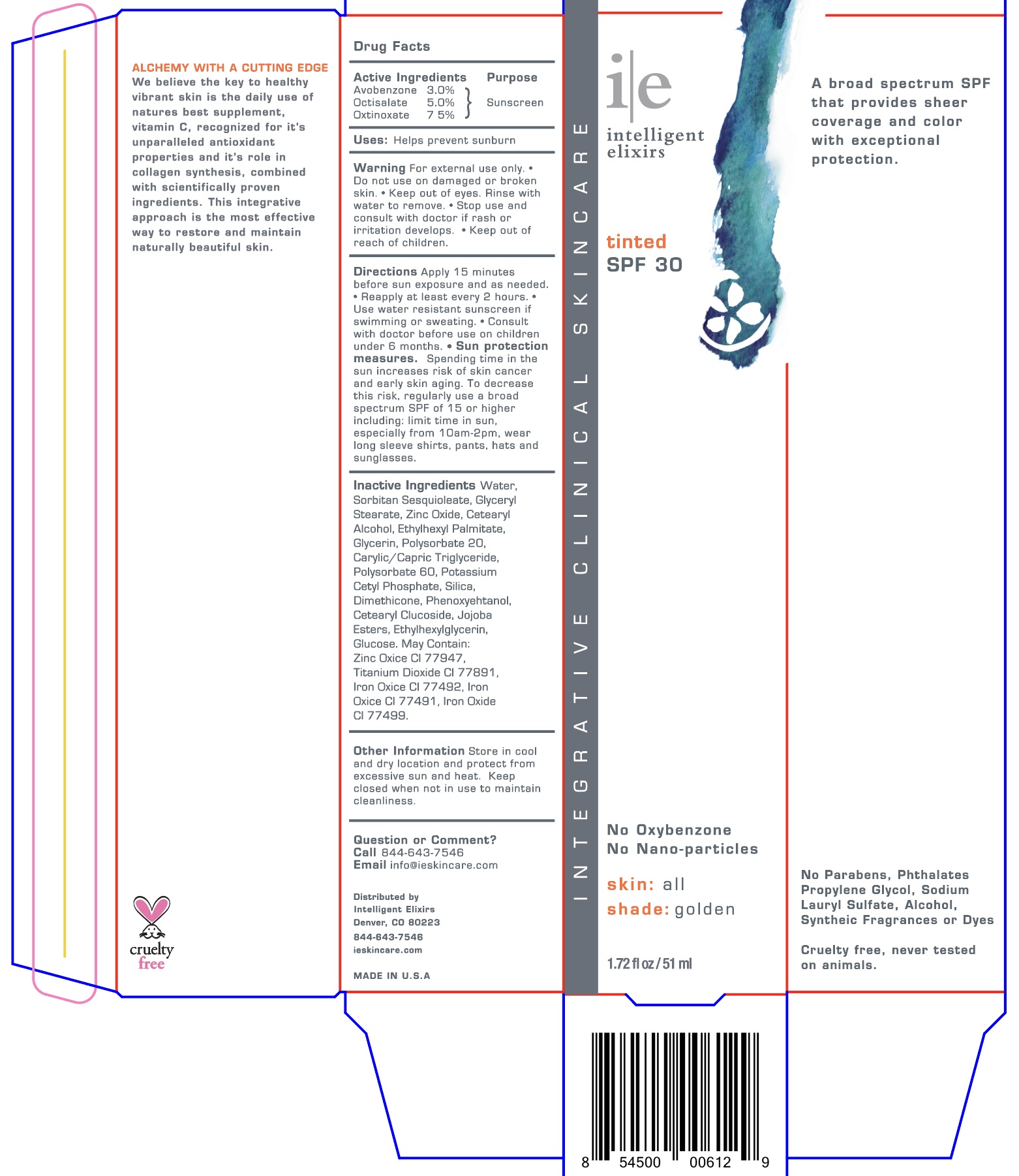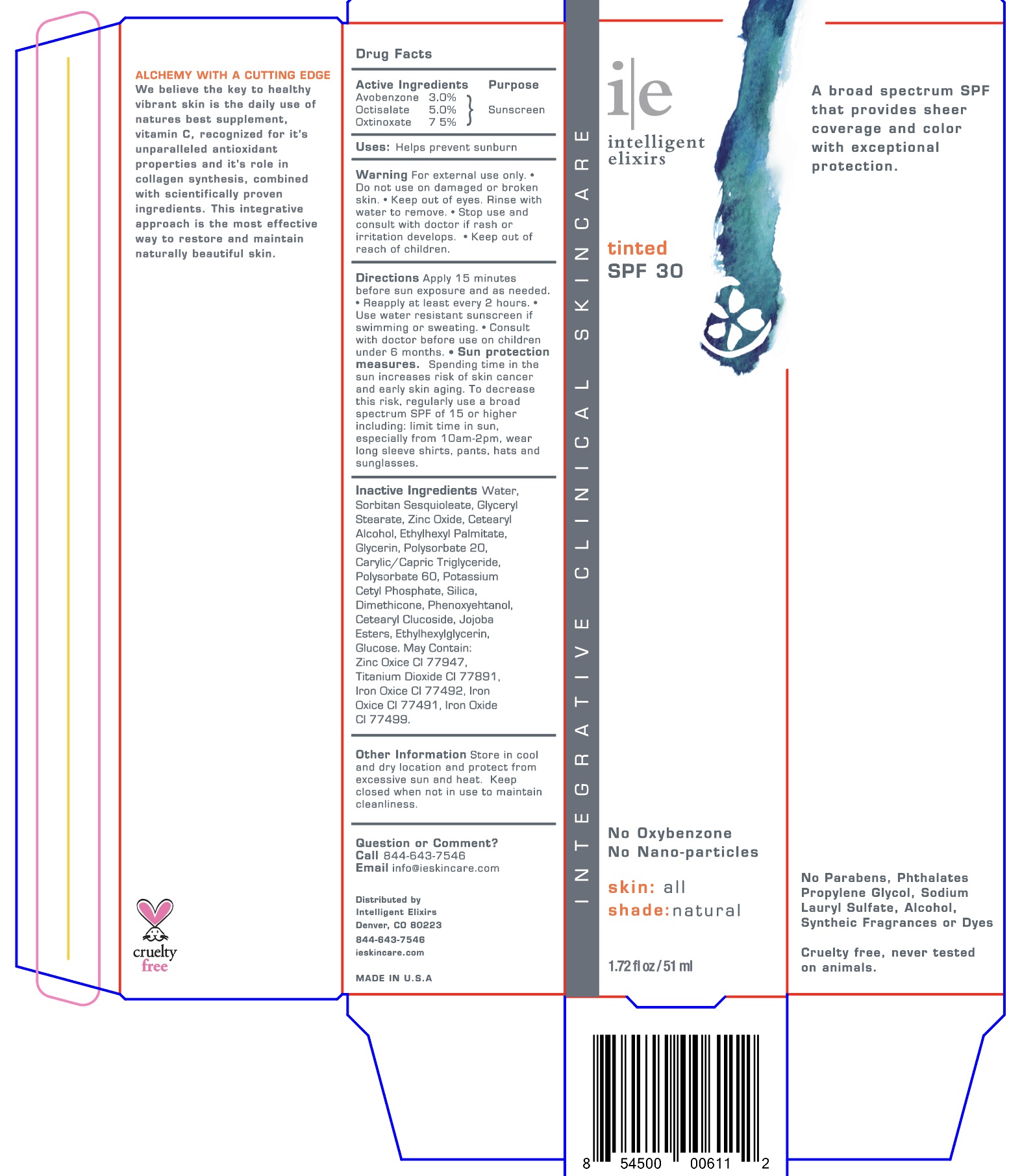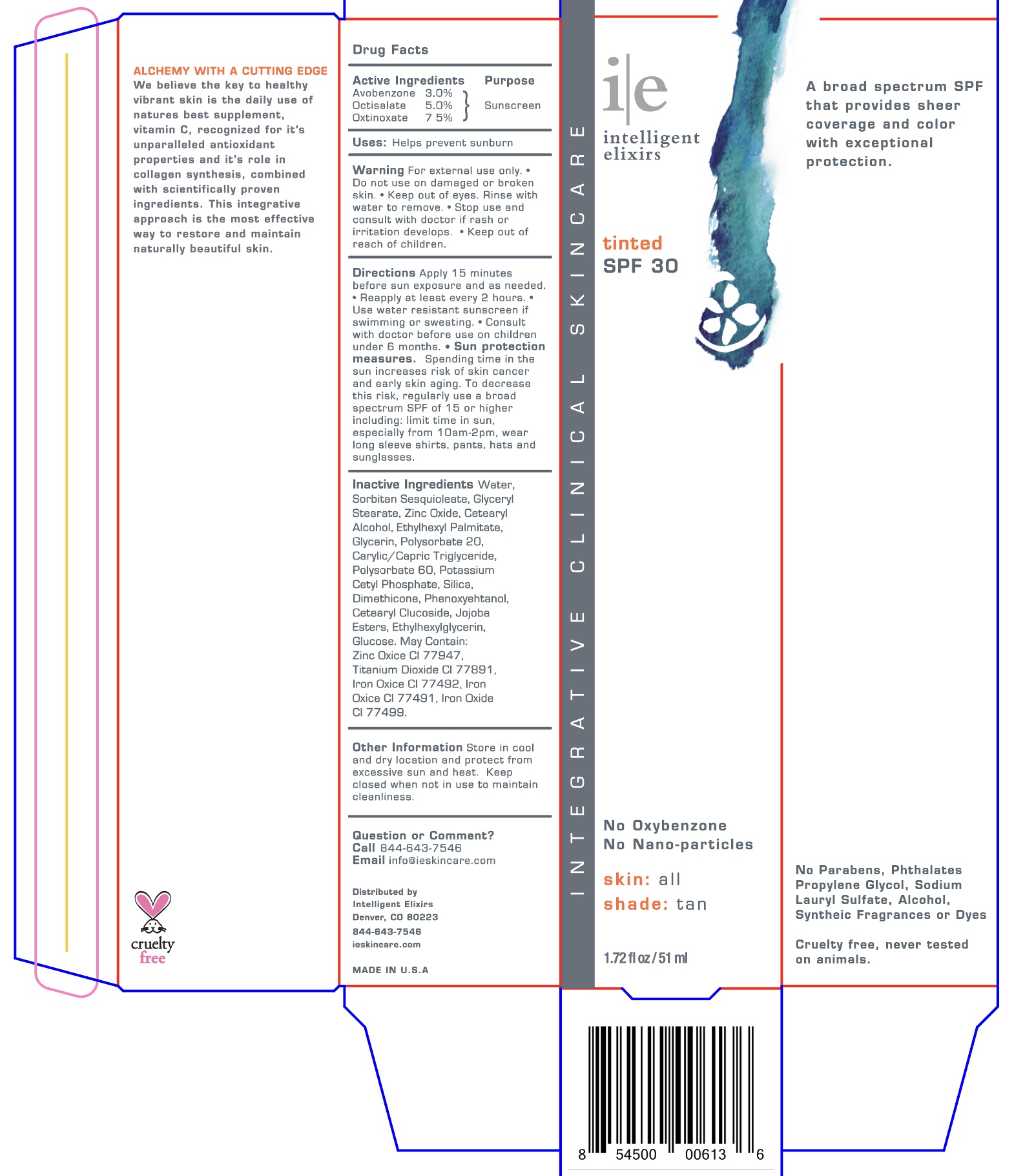 DRUG LABEL: Intelligent Elixirs Tinted Broad Spectrum SPF 30 - Natural
NDC: 84977-0031 | Form: LOTION
Manufacturer: Intelligent Elixirs, LLC
Category: otc | Type: HUMAN OTC DRUG LABEL
Date: 20251224

ACTIVE INGREDIENTS: OCTISALATE 5 g/100 mL; OCTINOXATE 7.5 g/100 mL; AVOBENZONE 3 g/100 mL
INACTIVE INGREDIENTS: CI 77491; CI 77492; DIMETHICONE; CAPRYLIC/CAPRIC TRIGLYCERIDE; GLUCOSE; GLYCERIN; ZINC OXIDE; ETHYLHEXYL PALMITATE; WATER; CETEARYL ALCOHOL; POLYSORBATE 20; POTASSIUM CETYL PHOSPHATE; SILICA; PHENOXYETHANOL; CETEARYL GLUCOSIDE; HYDROGENATED JOJOBA OIL/JOJOBA OIL, RANDOMIZED (IODINE VALUE 57-61); ETHYLHEXYLGLYCERIN; POLYSORBATE 60; SORBITAN SESQUIOLEATE; TITANIUM DIOXIDE; GLYCERYL STEARATE; CI 77499

Intelligent Elixirs Tinted Broad Spectrum SPF 30 - Natural / Golden / Tan (1.72 fl oz / 51 ml)

Active Ingredients

Avobenzone 3%
Octisalate 5%
Octinoxate 7.5%

Purpose

Sunscreen

Uses

Helps prevent sunburn

Warnings

For external use only

Do not use

on damaged or broken skin

When using this product

Keep out of eyes. Rinse with water to remove.

Stop use and consult with doctor if

rash or irritation develops.

Directions

Apply 15 minutes before sun exposure and as needed.
Reapply at least every 2 hours.

Use water resistant sunscreen if swimming or sweating.

Consult with doctor before use on children under 6 months.
Sun protection measures.
Spending time in the sun increases risk of skin cancer and early skin aging. To decrease this risk, regularly use a broad spectrum SPF of 15 or higher, including: limit time in sun, especially from 10am-2pm, wear long sleeve shirts, pants, hats and sunglasses.

Inactive Ingredients

Water, Zinc Oxide, Sorbitan Sesquioleate, Glyceryl Stearate, Cetearyl Alcohol, Ethylhexyl Palmitate, Glycerin, Polysorbate 20, Caprylic/Capric Triglyceride, Polysorbate 60, Potassium Cetyl Phosphate, Dimethicone, Silica, Phenoxyethanol, Cetearyl Glucoside, Jojoba Esters, Ethylhexylglycerin, Glucose. May contain: Titanium Dioxide CI 77891, Iron Oxide CI 77492, Iron Oxide CI 77491, Iron Oxide CI 77499.

Other Information

Store in cool and dry location and protect from excessive sun and heat. Keep closed when not in use to maintain cleanliness.

Question or Comment?

Call 844-643-7546
Email info@ieskincare.com

Principal Display Panel

i|e

intelligent
elixirs

tinted
SPF 30

No Oxybenzone
No Nano-particles

skin: all
shade: natural / golden / tan

1.72 fl oz / 51 ml